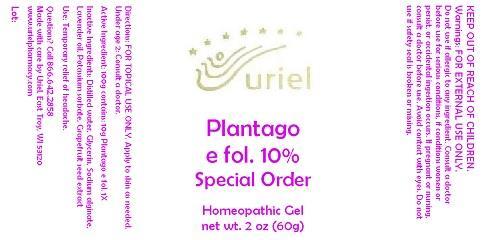 DRUG LABEL: Plantago e fol. 10 Special Order
NDC: 48951-8294 | Form: GEL
Manufacturer: Uriel Pharmacy Inc.
Category: homeopathic | Type: HUMAN OTC DRUG LABEL
Date: 20150122

ACTIVE INGREDIENTS: PLANTAGO MAJOR LEAF 1 [hp_X]/1 g
INACTIVE INGREDIENTS: WATER; GLYCERIN; SODIUM ALGINATE; LAVENDER OIL; POTASSIUM SORBATE; CITRUS PARADISI SEED

Plantago e fol. 10 Special Order

INDICATIONS AND USAGE

Directions: FOR TOPICAL USE ONLY.

DOSAGE AND ADMINISTRATION

Apply to skin as needed. Under age 2: Consult a doctor.

Active Ingredient: 100g contains: 10g Plantago e fol. 1X

INACTIVE INGREDIENT

Inactive Ingredients: Distilled water, Glycerin, Sodium alginate, Lavender oil, Potassium sorbate, Grapefruit seed extract

PURPOSE

Use: Temporary relief of headache.

KEEP OUT OF REACH OF CHILDREN.

WARNINGS

Warnings: FOR EXTERNAL USE ONLY. Do not use if allergic to any ingredient. Consult a doctor before use for serious conditions, if conditions worsen or persist, or accidental ingestion occurs. If pregnant or nursing, consult a doctor before use. Avoid contact with eyes. Do not use if safety seal is broken or missing.

QUESTIONS

Questions? Call 866.642.2858 Made with care by Uriel, East Troy, WI 53120 www.urielpharmacy.com